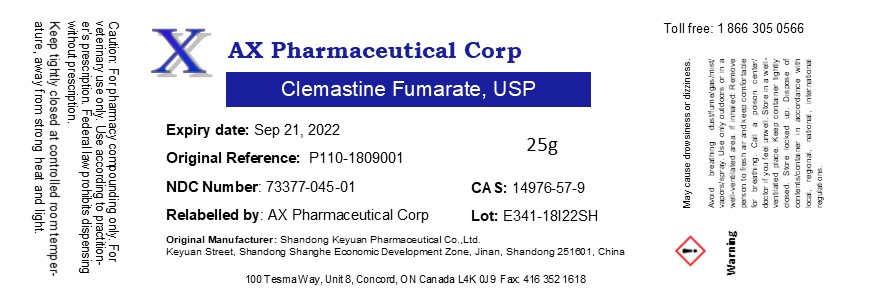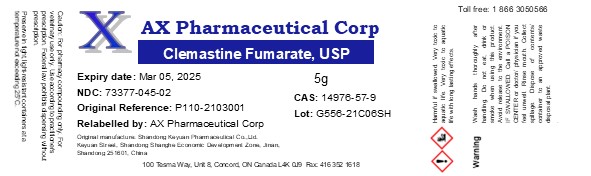 DRUG LABEL: Clemastine Fumarate
NDC: 73377-045 | Form: POWDER
Manufacturer: AX Pharmaceutical Corp
Category: other | Type: BULK INGREDIENT - ANIMAL DRUG
Date: 20260119

ACTIVE INGREDIENTS: CLEMASTINE FUMARATE 1 g/1 g

Clemastine Fumarate